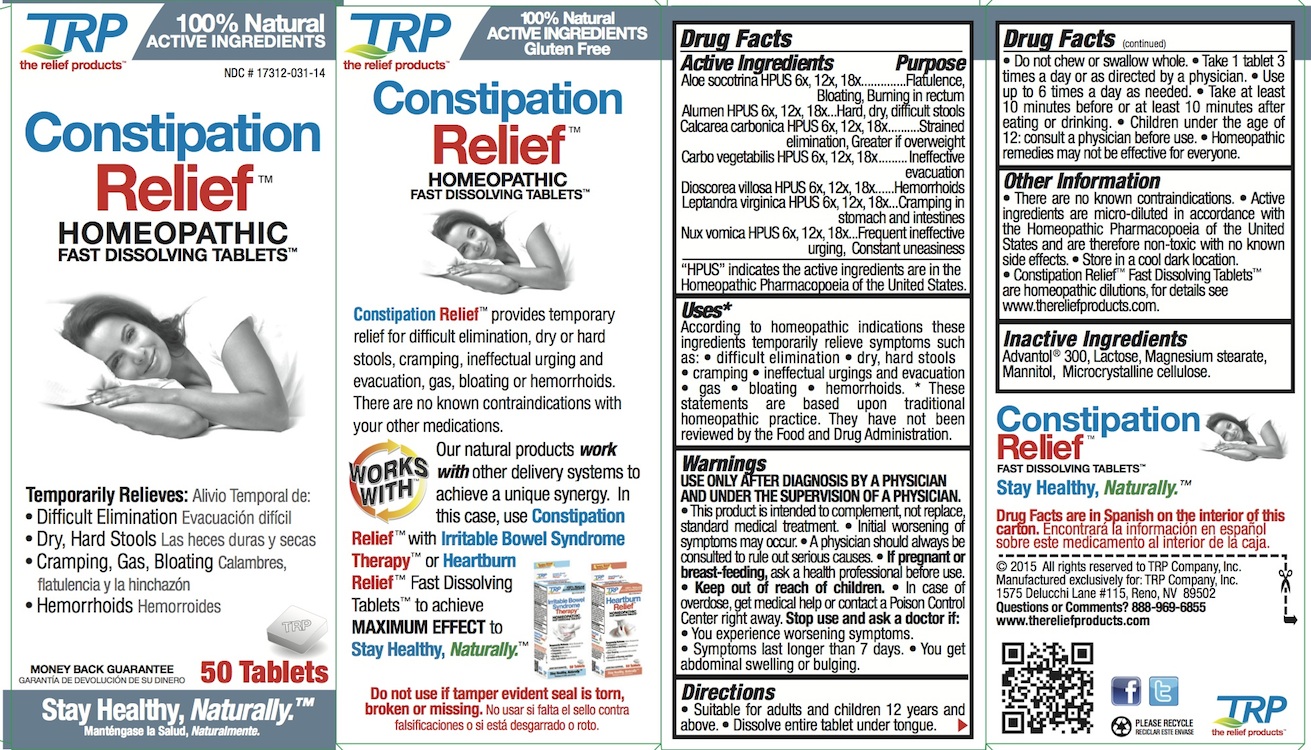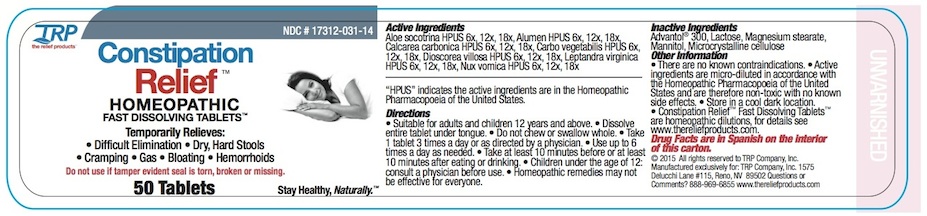 DRUG LABEL: Constipation Relief
NDC: 17312-031 | Form: TABLET, ORALLY DISINTEGRATING
Manufacturer: TRP Company
Category: homeopathic | Type: HUMAN OTC DRUG LABEL
Date: 20251215

ACTIVE INGREDIENTS: DIOSCOREA VILLOSA ROOT 6 [hp_X]/1 1; ACTIVATED CHARCOAL 6 [hp_X]/1 1; OYSTER SHELL CALCIUM CARBONATE, CRUDE 6 [hp_X]/1 1; POTASSIUM ALUM 6 [hp_X]/1 1; ALOE 6 [hp_X]/1 1; STRYCHNOS NUX-VOMICA SEED 6 [hp_X]/1 1; VERONICASTRUM VIRGINICUM ROOT 6 [hp_X]/1 1
INACTIVE INGREDIENTS: MANNITOL; SORBITOL; CROSPOVIDONE; CELLULOSE, MICROCRYSTALLINE; COPOVIDONE; SILICON DIOXIDE; LACTOSE; MAGNESIUM STEARATE

Constipation Relief™

PURPOSE

Aloe socotrina HPUS Flatulence, Bloating, Burning in rectum
Alumen HPUS Hard, dry, difficult stools
Calcarea carbonica HPUS Strained elimination, Greater if overweight
Carbo vegetabilis HPUS Ineffective evacuation
Dioscorea villosa HPUS Hemorrhoids
Leptandra virginica HPUS Cramping in stomach and intestines
Nux vomica HPUS Frequent ineffective urging, Constant uneasiness

Uses:*

According to homeopathic indications these ingredients temporarily relieve symptoms such as: • difficult elimination • dry, hard stools • cramping • ineffectual urgings and evacuation • gas • bloating • hemorrhoids. * These statements are based upon traditional homeopathic practice. They have not been reviewed by the Food and Drug Administration.

Warnings:

USE ONLY AFTER DIAGNOSIS BY A PHYSICIAN AND UNDER THE SUPERVISION OF A PHYSICIAN.

- This product is intended to complement, not replace, standard medical treatment.
- Initial worsening of symptoms may occur.
- A physician should always be consulted to rule out serious causes.

PREGNANCY OR BREAST FEEDING

If pregnant or breast-feeding, ask a health professional before use.

Keep out of reach of children

In case of overdose, get medical help or contact a Poison Control Center right away.

Directions

- Suitable for adults and children 12 years and above.
- Dissolve entire tablet under tongue.
- Do not chew or swallow whole.
- Take 1 tablet 3 times a day or as directed by a physician.
- Use up to 6 times a day as needed.
- Take at least 10 minutes before or at least 10 minutes after eating or drinking.
- Children under the age of 12: consult a physician before use.

Homeopathic remedies may not be effective for everyone.

Inactive Ingredients

Advantol® 300, Lactose, Magnesium Stearate, Mannitol, Microcrystalline Cellulose.

QUESTIONS

www.thereliefproducts.com, 1-888-969-6855

Active Ingredients

Aloe socotrina HPUS 6x 12x 18x

Alumen HPUS 6x 12x 18x

Calcarea carbonica HPUS 6x 12x 18x

Carbo vegetabilis HPUS 6x 12x 18x

Dioscorea villosa HPUS 6x 12x 18x

Leptandra virginica HPUS 6x 12x 18x

Nux vomica HPUS 6x 12x 18x

HPUS indicates the active ingredients are in the Homeopathic Pharmacopoeia of the United States.

Stop Use

Stop use and ask a doctor if:

- You experience worsening symptoms.
- If symptoms last longer than 7 days.
- You get abdominal swelling or bulging.

- There are no known contraindications.
- Active ingredients are micro-diluted in accordance with the Homeopathic Pharmacopoeia of the United States and are therefore non-toxic with no known side effects.
- Store in a cool dark location.

Constipation Relief ™ Homeopathic Fast Dissolving Tablet are homeopathic dilutions: see www.thereliefproducts.com for details.